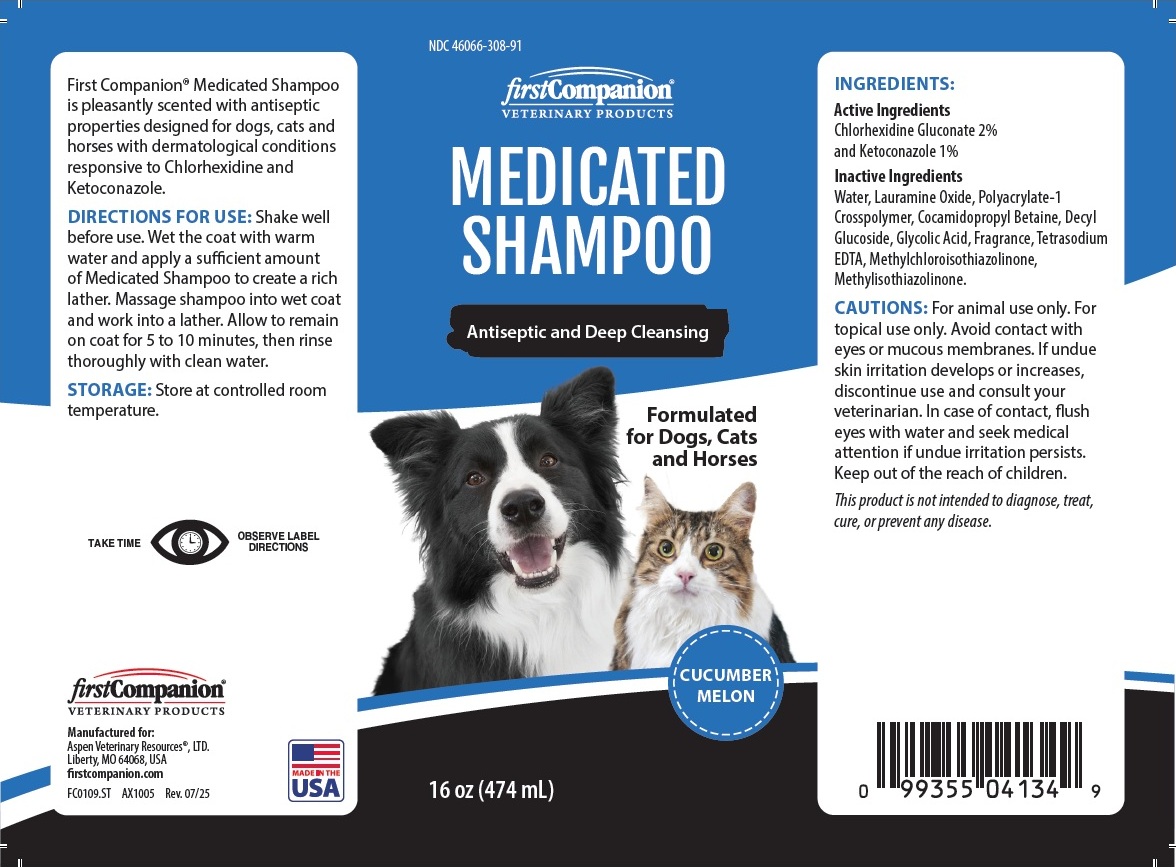 DRUG LABEL: firstCompanion MEDICATED
NDC: 46066-308 | Form: SHAMPOO
Manufacturer: Aspen Veterinary Resources, Ltd.
Category: animal | Type: OTC ANIMAL DRUG LABEL
Date: 20250925

ACTIVE INGREDIENTS: CHLORHEXIDINE GLUCONATE 2 g/100 mL; KETOCONAZOLE 1 g/100 mL
INACTIVE INGREDIENTS: WATER; LAURAMINE OXIDE; POLYACRYLATE-1 CROSSPOLYMER; COCAMIDOPROPYL BETAINE; DECYL GLUCOSIDE; GLYCOLIC ACID; EDETATE SODIUM; METHYLCHLOROISOTHIAZOLINONE; METHYLISOTHIAZOLINONE

firstCompanion® VETERINARY PRODUCTS MEDICATED SHAMPOO

Active Ingredients

Chlorhexidine Gluconate 2%
and Ketoconazole 1%

Inactive Ingredients

Water, Lauramine Oxide, Polyacrylate-1 Crosspolymer, Cocamidopropyl Betaine, Decyl Glucoside, Glycolic Acid, Fragrance, Tetrasodium EDTA, Methylchloroisothiazolinone, Methylisothiazolinone.

CAUTIONS:

For animal use only. For topical use only. Avoid contact with eyes or mucous membranes. If undue skin irritation develops or increases, discontinue use and consult your veterinarian. In case of contact, flush eyes with water and seek medical attention if undue irritation persists. Keep out of the reach of children.
This product is not intended to diagnose, treat, cure, or prevent any disease.

DIRECTIONS FOR USE:

Shake well before use. Wet the coat with warm water and apply a sufficient amount of Medicated Shampoo to create a rich lather. Massage shampoo into wet coat and work into a lather. Allow to remain on coat for 5 to 10 minutes, then rinse thoroughly with clean water.

STORAGE:

Store at controlled room temperature.

Antiseptic and Deep Cleansing

Formulated for Dogs, Cats and Horses

CUCUMBER
MELON

First Companion® Medicated Shampoo is pleasantly scented with antiseptic properties designed for dogs, cats and horses with dermatological conditions responsive to Chlorhexidine and Ketoconazole.

TAKE TIME

OBSERVE LABEL DIRECTIONS

Manufactured for:
Aspen Veterinary Resources®, LTD.
Liberty, MO 64068, USA

firstcompanion.com

MADE IN THE USA